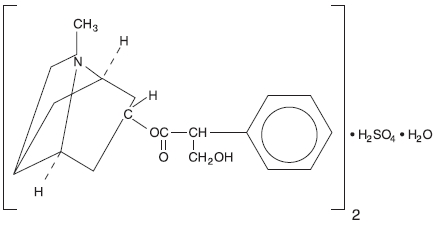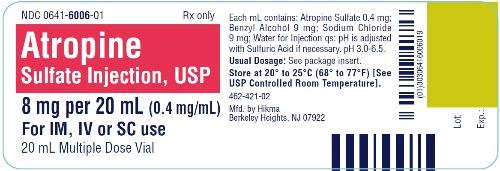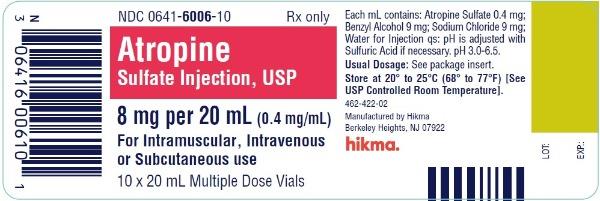 DRUG LABEL: Atropine Sulfate
NDC: 0641-6006 | Form: INJECTION
Manufacturer: Hikma Pharmaceuticals USA Inc.
Category: prescription | Type: HUMAN PRESCRIPTION DRUG LABEL
Date: 20240408

ACTIVE INGREDIENTS: ATROPINE SULFATE 0.4 mg/1 mL
INACTIVE INGREDIENTS: SODIUM CHLORIDE 9 mg/1 mL; BENZYL ALCOHOL 9 mg/1 mL; WATER; SULFURIC ACID

Atropine Sulfate Injection, USP

For Intramuscular, Intravenous or Subcutaneous use

RX only

DESCRIPTION

Atropine Sulfate Injection, USP is a sterile solution of atropine sulfate in Water for Injection. Each mL contains Atropine Sulfate 0.4 mg; Sodium Chloride 9 mg; Benzyl Alcohol 9 mg; Water for Injection qs; pH may be adjusted with Sulfuric Acid if necessary. pH 3.0-6.5.
Atropine Sulfate Injection, USP may be given intramuscularly, intravenously or subcutaneously. Atropine is a white crystalline alkaloid which may be extracted from belladonna root or may be produced synthetically. It is used as atropine sulfate because this compound has much greater solubility.
Atropine sulfate is an anticholinergic drug. The empirical formula of atropine sulfate is (C17H23NO3)2•H2SO4•H2O.
The structural formula is:

CLINICAL PHARMACOLOGY

The most important therapeutic action of atropine is the inhibition of smooth muscle and glands innervated by postganglionic cholinergic nerves. It also has central nervous system activity, which may be stimulating or depressing depending upon the dose.
Following the administration of usual clinical doses, atropine produces stimulation of the medulla and higher cerebral centers. This effect is manifested by mild central vagal excitation and moderate respiratory stimulation. Atropine sulfate also acts peripherally as a competitive antagonist of the muscarinic actions of acetylcholine. It does not prevent the release of acetylcholine but antagonizes the effect of acetylcholine on the effector cells.
These actions include vasodilation, drying of the mouth, an increase in the pulse rate, inhibition of contractions of the gastrointestinal tract, ureter, and bladder, and reduction of salivary, bronchial, gastric and sweat gland secretions. Following clinical and larger doses, atropine sulfate causes dilation of the pupils and paralysis of accommodation and, in narrow-angle glaucoma, can increase intraocular pressure.

INDICATIONS AND USAGE

Atropine sulfate is given parenterally as a preanesthetic medication to decrease salivation and bronchial secretions. It is useful in pylorospasm and other spastic conditions of the gastrointestinal tract. For ureteral and biliary colic, atropine sulfate given with morphine may be indicated. Atropine sulfate is indicated for relaxation of the upper gastrointestinal tract and colon during hypotonic radiography.
Atropine is used as an antidote for pilocarpine, physostigmine, isoflurophate, choline esters, certain species of aminata and in poisoning by the organic phosphate cholinesterase inhibitors found in certain insecticides and by chemical warfare “nerve gases”. Large doses relieve the muscarine-like symptoms and some of the central nervous system manifestations.

CONTRAINDICATIONS

Conditions at which inhibition of postganglionic cholinergic nerves are undesirable, such as glaucoma and tachycardia. Also contraindicated in asthma, because the parenteral dose which might relieve asthma would have an excessive drying effect upon mucous plugs in the bronchi. Prostatic hypertrophy, while not a contraindication, requires special attention to signs of urinary retention.

WARNINGS

Atropine is a highly potent drug and due care is essential to avoid overdosage, especially with intravenous administration. Pediatric populations are more susceptible than adults to the toxic effects of anticholinergic agents.
Atropine I.V. decreased the rate of mexiletine absorption without altering the relative oral bioavailability; this delay in mexiletine absorption was reversed by the combination of atropine and intravenous metoclopramide during pretreatment for anesthesia. Atropine is not removed by dialysis.
This drug is effective in very low dosage and overdose may cause permanent damage or death, especially in children.
This product contains Benzyl Alcohol which has been associated with a fatal gasping syndrome in infants and neonates.

PRECAUTIONS

General

Doses of 0.5 to 1 mg atropine are mildly stimulating to the CNS. Larger doses may produce mental disturbances; still larger doses are depressing. Death from atropine poisoning, though rare, is usually due to paralysis of the medullary centers.

Information for Patients

Atropine causes dryness of the mouth, and when used with other drugs that can cause dryness of the mouth, the effect is additive. Patients receiving chronic treatment can develop blurred vision, and they should not be involved in activities that require good and clear vision.

Drug Interactions

Atropine, by slowing gastric emptying and gastrointestinal mobility, may interfere with the absorption of other medications. The effect of atropine on dryness of the mouth may be increased if it is given with other drugs that have anticholinergic action.

Pregnancy Category C

Animal reproduction studies have not been conducted with atropine sulfate. It is also not known whether atropine sulfate can cause fetal harm when administered to a pregnant woman or can affect reproduction capacity. Atropine sulfate should be given to a pregnant woman only if clearly needed.

Nursing Mothers

Caution should be exercised when atropine sulfate is administered to a nursing mother.

ADVERSE REACTIONS

Individual tolerance varies greatly, but these systemic doses are likely to produce the following effects:

0.5 mg - | Slight dryness of nose and mouth, bradycardia.
1 mg - | Greater dryness of nose and mouth, with thirst; slowing, then acceleration of heart; slight mydriasis.
2 mg - | Very dry mouth, tachycardia, with palpitation, mydriasis, slight blurring of near vision.
5 mg - | Increase in the above symptoms plus disturbance of speech, difficulty in swallowing, headache, hot, dry skin, restlessness with asthenia.
10 mg and over - | Above symptoms to extreme degree, plus ataxia, excitement, disorentation, hallucinations, delirium and coma.
65 mg - | May be fatal.

A scarlatiniform rash may occur. Atropine may produce fever, particularly in children, through inhibition of heat loss by evaporation. Although large doses of atropine may cause an alarming condition, recovery is usual.

OVERDOSAGE

Toxic doses from atropine are not uncommon, especially in children.

Symptoms

The principle manifestations of poisoning with atropine are delirium, tachycardia and fever.

Treatment

In the treatment of atropine poisoning, respiratory assistance and symptomatic support are indicated. Physostigmine salicylate, 1 to 5 mL of a dilution containing 1 mg per 5 mL of saline, should be administered intravenously. Administer the smaller dose in children and administer in not less than 2 minutes. Monitor with ECG. Medication can be repeated every 5 minutes for a total dose of 2 mg in children and every 30 minutes for a total dose of 6 mg in adults.
The fatal dose of atropine in children may be as low as 10 mg. In an adult, recovery after 1,000 mg of atropine sulfate has been reported. Death is usually due to paralysis of the medullary centers. The fatality rate is less than 1%. If the patient survives 24 hours, they will probably recover.

DOSAGE AND ADMINISTRATION

The usual dose of atropine sulfate is 0.4 to 0.6 mg. Suggested dosages for pediatric patients are as follows:
7 - 16 lbs. – 0.1 mg 40 - 65 lbs. – 0.3 mg
17 - 24 lbs. – 0.15 mg 65 - 90 lbs. – 0.4 mg
24 - 40 lbs. – 0.2 mg Over 90 lbs. – 0.4 to 0.6 mg

Table of Dosage Equivalents
Atropine Sulfate Solution (mL required)
mg required | 1 mg per mL | 0.4 mg per mL
1 | 1
0.80 | 0.80
0.60 | 0.60
0.50 | 0.50
0.40 | 0.40 | 1
0.30 | 0.30 | 0.75
0.25 | 0.25 | 0.63
0.20 | 0.20 | 0.50
0.18 | 0.18 | 0.45
0.15 | 0.15 | 0.38
0.12 | 0.12 | 0.30
0.10 | 0.10 | 0.25

These doses may be exceeded in certain cases.
For hypotonic radiography of the gastrointestinal tract, the usual adult dose is 1 mg intramuscularly.
Adults suspected of contact with organic phosporous insecticides of the parathion type should be given atropine sulfate 0.8 mg intramuscularly. If an atropine effect is not apparent within 30 minutes or if definite symptoms of the poisoning occur (nausea, vomiting, diarrhea, pupillary constriction, pulmonary edema, fasciculations of eyelids and tongue, jerky ocular movements and excessive sweating, salivation and bronchial secretion), atropine sulfate 2 mg should be given intramuscularly at hourly intervals until signs of atropinization are observed. Up to 2 or 3 times of this dose (4 to 6 mg) may be required in severe cases.

Parenteral drug products should be inspected visually for particulate matter and discoloration prior to administration, whenever solution and container permit.

HOW SUPPLIED

Atropine Sulfate Injection, USP is available in the following:
0.4 mg/mL
20 mL multiple dose vial packaged in 10s (NDC 0641-6006-10)
Use only if solution is clear and seal intact.
Store at 20° to 25°C (68° to 77°F), excursions permitted to 15° to 30°C (59° to 86°F) [See USP Controlled Room Temperature].

To report SUSPECTED ADVERSE REACTIONS, contact Hikma Pharmaceuticals USA Inc. at 1-877-845-0689, or the FDA at 1-800-FDA-1088 or www.fda.gov/medwatch.

For Product Inquiry call 1-877-845-0689.

Manufactured by:
Hikma Pharmaceuticals USA Inc.
Berkeley Heights, NJ 07922

Revised May 2020

462-416-02

PRINCIPAL DISPLAY PANEL

NDC 0641-6006-01 Rx only
Atropine
Sulfate Injection, USP
8 mg per 20 mL (0.4 mg/mL)
For IM, IV or SC use
20 mL Multiple Dose Vial

NDC 0641-6006-10 Rx only
Atropine
Sulfate Injection, USP
8 mg per 20 mL (0.4 mg/mL)
For Intramuscular, Intravenous
or Subcutaneous use
10 x 20 mL Multiple Dose Vials